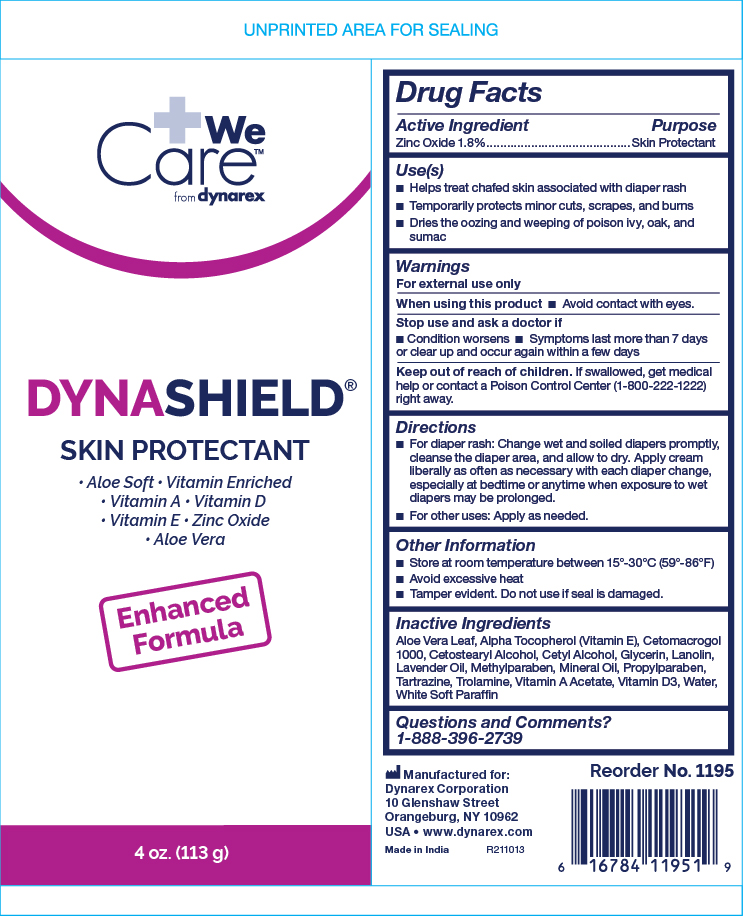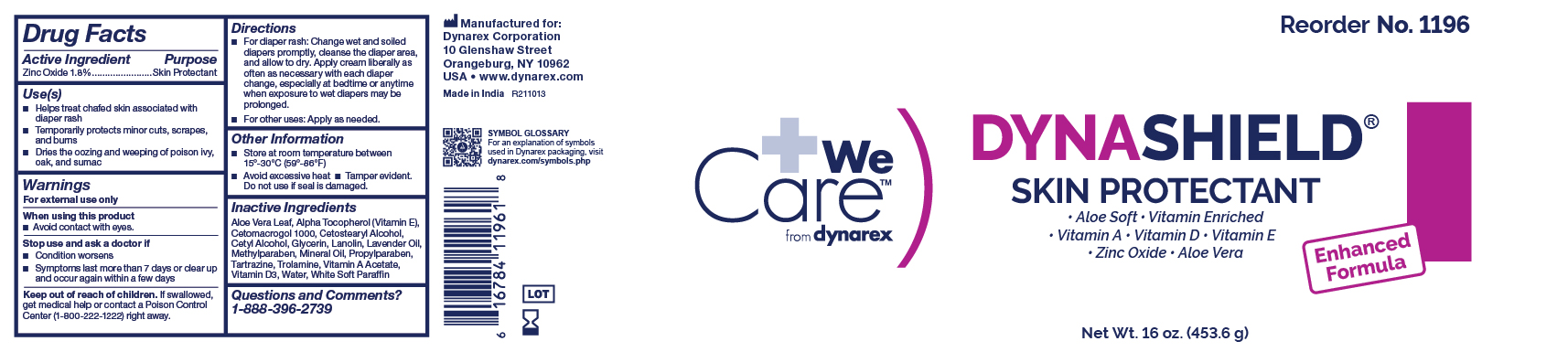 DRUG LABEL: Dynashield
NDC: 67777-407 | Form: CREAM
Manufacturer: Dynarex Corporation
Category: otc | Type: HUMAN OTC DRUG LABEL
Date: 20241120

ACTIVE INGREDIENTS: ZINC OXIDE 1.8 g/100 g
INACTIVE INGREDIENTS: VITAMIN A ACETATE; FD&C YELLOW NO. 5; LAVENDER OIL; ALPHA-TOCOPHEROL; ALOE VERA LEAF; TROLAMINE; WATER; LANOLIN; CETETH-20; MINERAL OIL; METHYLPARABEN; PROPYLPARABEN; GLYCERIN; CETYL ALCOHOL; CETOSTEARYL ALCOHOL; CHOLECALCIFEROL; WHITE PETROLATUM

1195, 1196

Active Ingredient

Zinc Oxide 1.8%

Purpose

Skin Protectant

Uses

- Helps treat chafed skin associated with diaper rash
- Temporarily protects minor • cuts • scrapes • burns
- Dries the oozing and weeping of poison ivy, oak, sumac

Warnings

For External Use Only

When using this product

- Do not get in eyes

Stop use and ask a doctor if

- Condition worsens
- Symptoms last more than 7 days or clear up and occur again within a few days

Keep out of reach of children. If swallowed, get medical help or contact a Poison Control Center (1-800-222-1222) right away.

Directions

- For diaper rash: Change wet and soiled diapers promptly, cleanse the diaper area, and allow to dry. Apply cream liberally as often as necessary, with each diaper change, especially at bedtime or anytime when exposure to wet diapers may be prolonged.
- For other uses: Apply as needed.

Other Information

- Store at room temperature between 15º-30ºC (59°-86°F)
- Avoid excessive heat
- Tamper evident. Do not use if seal is damaged.

Inactive Ingredients

Glycerin, Cetostearyl Alcohol, Cetyl Alcohol, White Soft Paraffin, Mineral Oil, Lanolin, Cetomacrogol 1000, Aloe Vera Leaf, Methyl Paraben, Propyl Paraben, Perfume Lavander Oil, Alpha Tocopherol, Trolamine, Vitamin A Acetate, Cholecalciferol (Vitamin D3), FD&C Yellow No. 5 (Tartrazine), Water